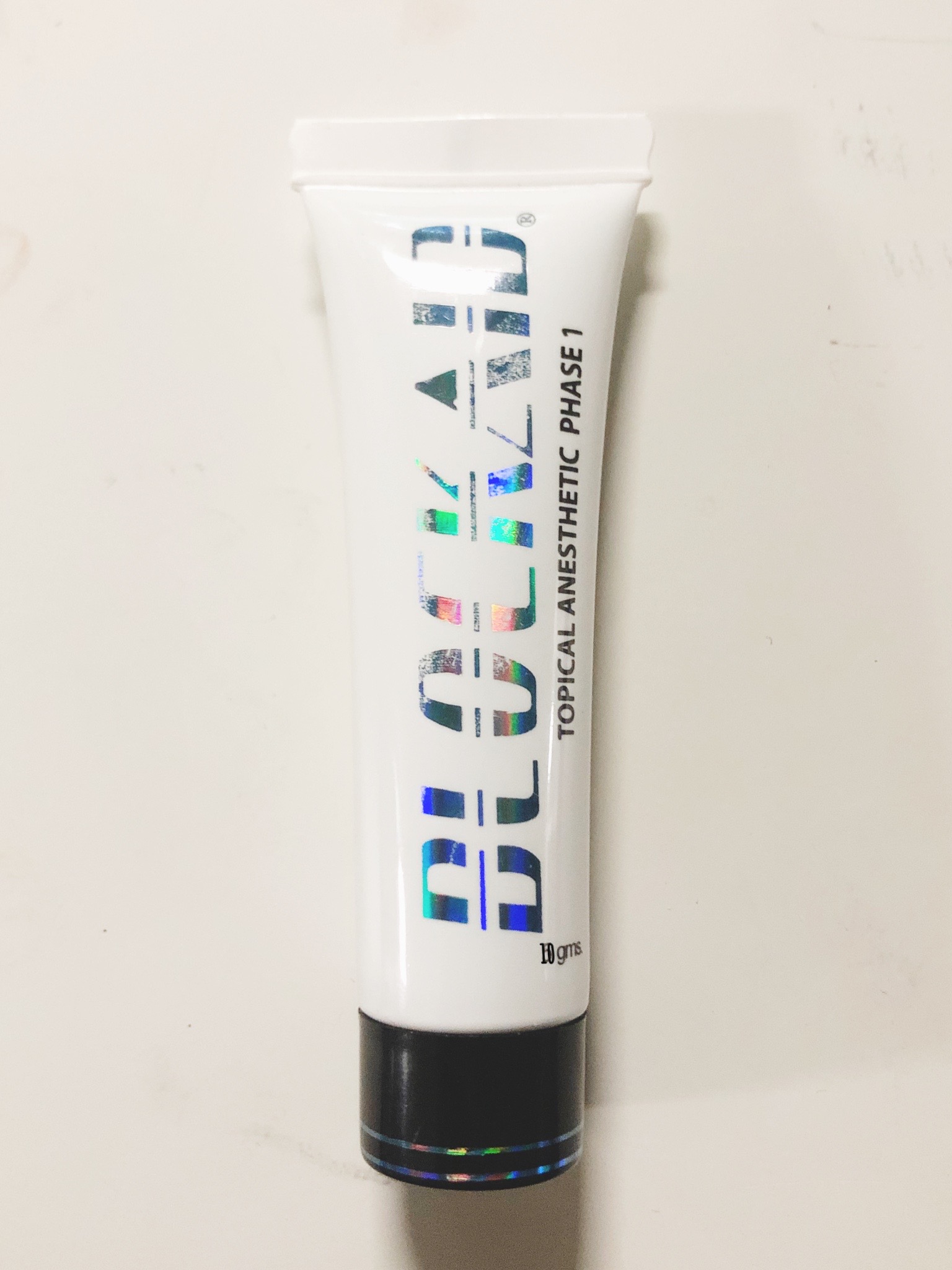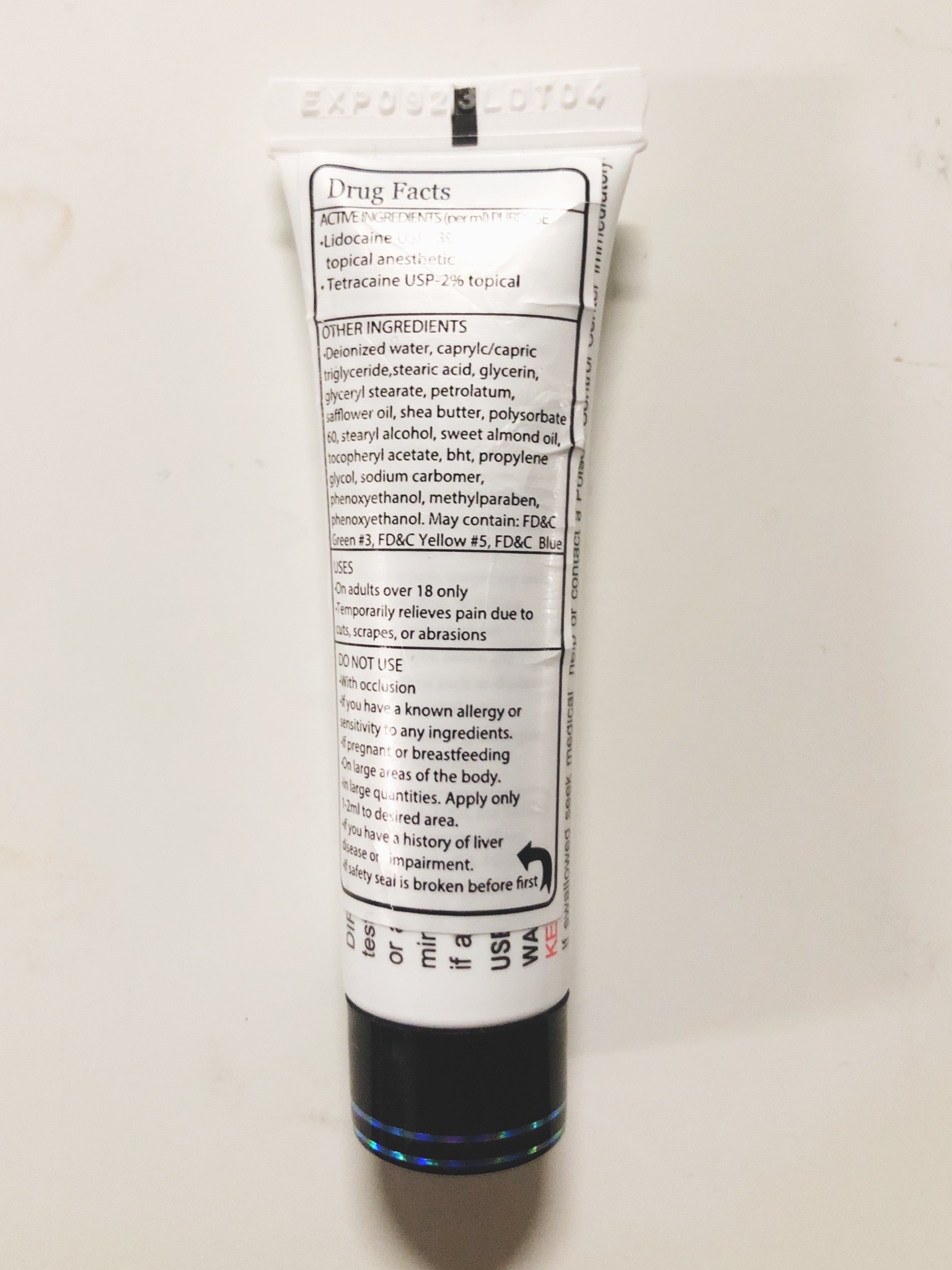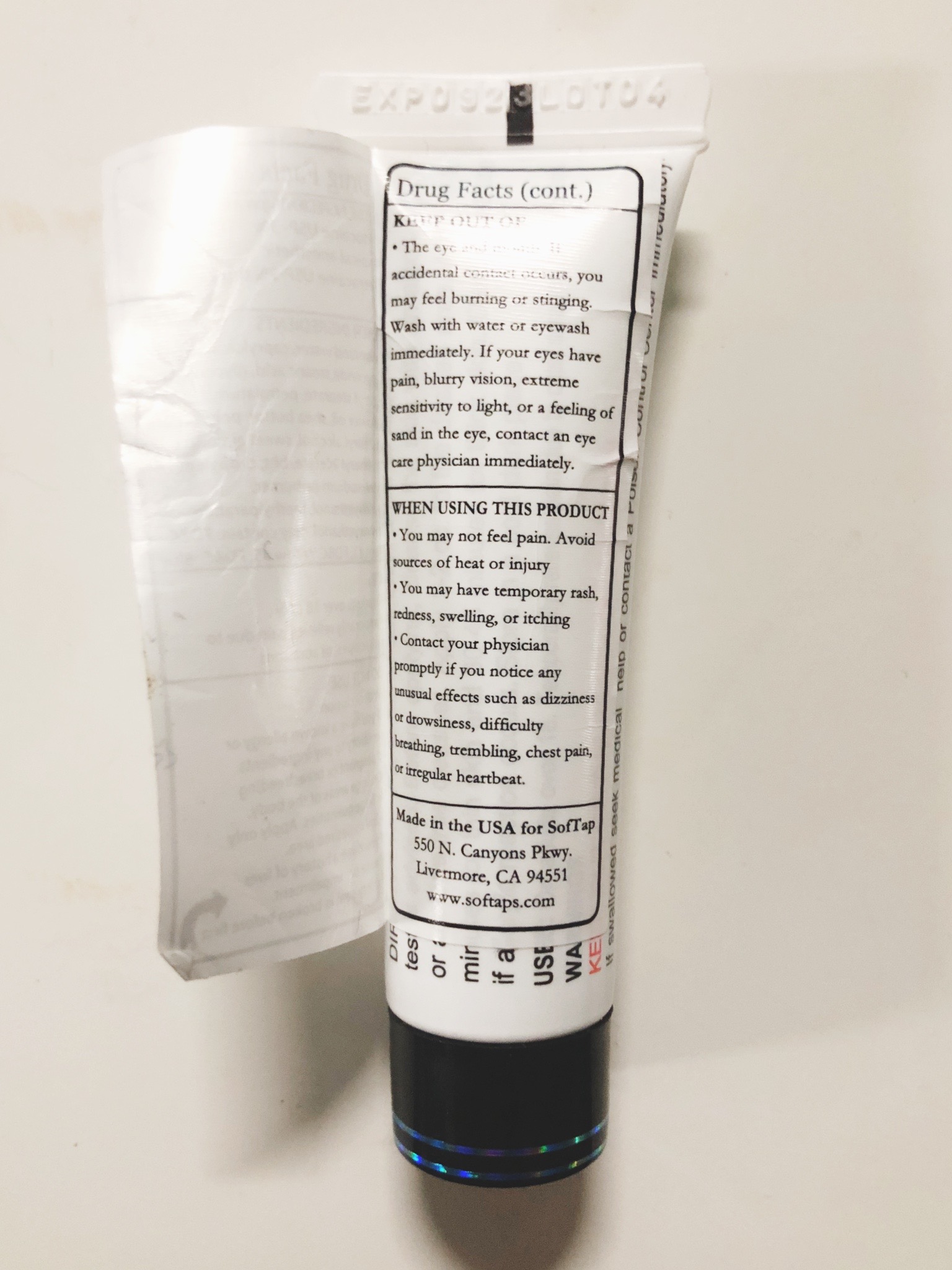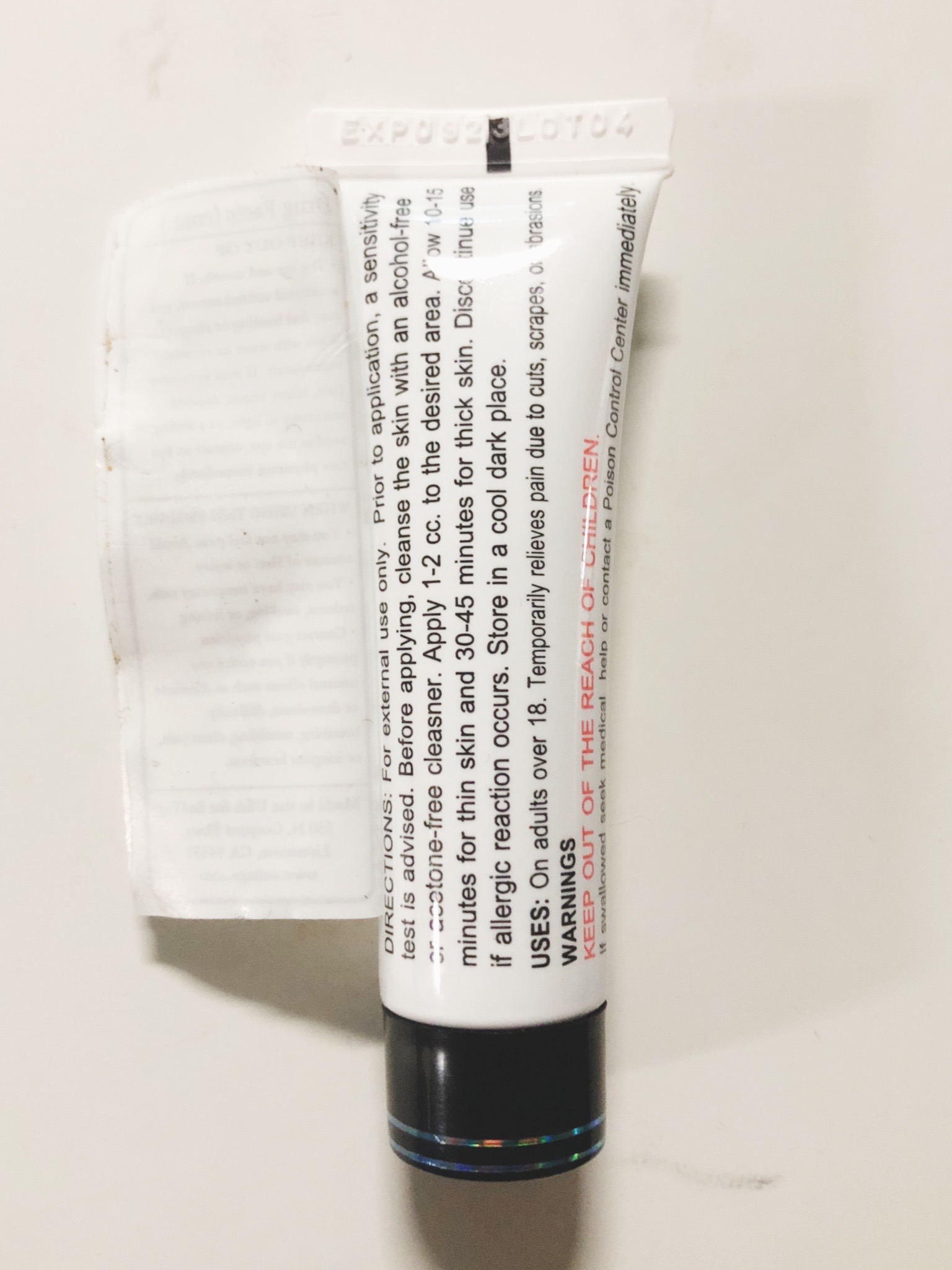 DRUG LABEL: Blockaid
NDC: 82718-1110 | Form: CREAM
Manufacturer: SofTap Inc
Category: otc | Type: HUMAN OTC DRUG LABEL
Date: 20220506

ACTIVE INGREDIENTS: TETRACAINE 0.02 g/10 g; LIDOCAINE 0.03 g/10 g
INACTIVE INGREDIENTS: WATER; PHENOXYETHANOL; FD&C BLUE NO. 1; METHYLPARABEN; FD&C GREEN NO. 3; FD&C YELLOW NO. 5; SODIUM CARBONATE; MEDIUM-CHAIN TRIGLYCERIDES; GLYCERIN; PETROLATUM; STEARIC ACID; STEARYL ALCOHOL; BUTYLATED HYDROXYTOLUENE; ALMOND OIL; PROPYLPARABEN; SAFFLOWER OIL; SHEA BUTTER; .ALPHA.-TOCOPHEROL ACETATE; GLYCERYL STEARATE SE; POLYSORBATE 60; PROPYLENE GLYCOL

DRUG FACTS

ACTIVE INGREDIENTS (per ml) PURPOSE

- Lidocaine USP - 3%

topical anesthetic

- Tetracaine USP - 2%

topical anesthetic

PURPOSE

- Lidocaine USP - 3%

topical anesthetic

- Tetracaine USP - 2%

topical anesthetic

OTHER INGREDIENTS

Deionized water, caprylc/capric triglyceride,stearic acid, glycerin, glyceryl stearate, petrolatum, safflower oil, shea butter, polysorbate 60, stearyl alcohol, sweet almond oil, tocopheryl acetate, bht, propylene glycol, sodium carbonate, phenoxyethanol, methylparaben, polyparaben. May contain: FD&C Green #3, FD&C Yellow #5, FD&C Blue #1

USES

- On adults over 18 only
- Temporarily relieves pain due to cuts, scrapes, or abrasions

DO NOT USE

- With occlusion
- If you have a known allergy or sensitivity to any ingredients
- If pregnant or breastfeeding
- On large areas of the body
- In large quantities. Apply only 1-2ml to desired area
- If you have a history of liver disease or impairment
- If safety seal is broken before first use

KEEP OUT OF

The eye and mouth. If accidental contact occurs, you may feel burning or stinging. Wash with water or eyewash immediately. If your eyes have pain, blurry vision, extreme sensitivity to light, or a feeling of sand in the eye, contact an eye care physician immediately.

WHEN USING THIS PRODUCT

You may not feel pain. Avoid sources of heat or injury.
You may have temporary rash, redness, swelling, or itching
Contact your physician promptly if you notice any unusual effects such as dizziness or drowsiness, difficulty breathing, trembling, chest pain, or irregular heartbeat.

Made in the USA for SofTap

550 N Canyons Pkwy

Livermore, CA 94551

www.softaps.com

DIRECTIONS

For external use only. Prior to application, a sensitivity test is advised. Before applying, cleanse the skin with an alcohol-free or acetone-free cleanser. Apply 1-2 cc to the desired area for up to 6 times per day. Discontinue use if allergic reaction occurs. Store in a cool dark place (up to 80 degrees F) or refrigerate.

WARNINGS

KEEP OUT OF REACH OF CHILDREN

WARNINGS

If swallowed seek medical help or contact a Poison Control Center immediately

BLOCKAID

TOPICAL ANESTHETIC PHASE I

10 gms